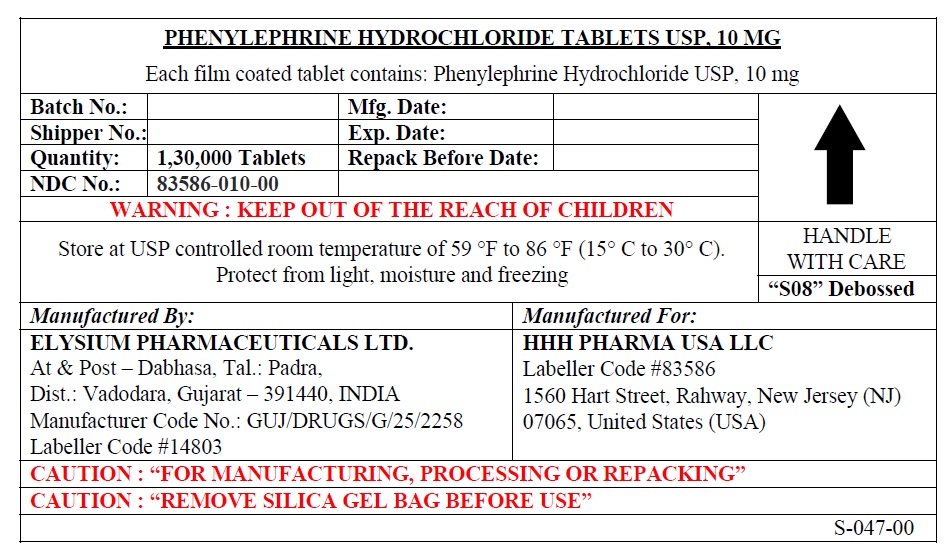 DRUG LABEL: PHENYLEPHRINE HYDROCHLORIDE
NDC: 83586-010 | Form: TABLET
Manufacturer: HHH PHARMA USA LLC
Category: otc | Type: HUMAN OTC DRUG LABEL
Date: 20250910

ACTIVE INGREDIENTS: PHENYLEPHRINE HYDROCHLORIDE 10 mg/1 1
INACTIVE INGREDIENTS: CROSCARMELLOSE SODIUM; SILICON DIOXIDE; DICALCIUM PHOSPHATE; FD&C RED NO. 40; MAGNESIUM STEARATE; MICROCRYSTALLINE CELLULOSE

Active Ingredient (in each caplet)

Phenylephrine HCl USP 10 mg

Purpose

Nasal decongestant

Uses

- temporarily relieves nasal congestion due to the common cold, hay fever or other upper respiratory allergies
- temporarily relieves sinus congestion and pressure

Warnings

Do not use if you are now taking a prescription monoamine oxidase inhibitor (MAOI) (certain drugs for depression, psychiatric or emotional conditions, or Parkinson's disease), or for 2 weeks after stopping the MAOI drug. If you do not know if your prescription drug contains an MAOI, ask a doctor or pharmacist before taking this product.

Ask a doctor before use if you have

- heart disease
- high blood pressure
- thyroid disease
- diabetes
- trouble urinating due to an enlarged prostate gland.

When using this product do not exceed recommended dose.

Stop use and ask a doctor if

- nervousness, dizziness, or sleeplessness occur
- symptoms do not improve within 7 days or occur with a fever.

PREGNANCY OR BREAST FEEDING

If pregnant or breast-feeding, ask a health professional before use.

Keep out of reach of children. In case of overdose, get medical help or contact a Poison Control Center (1-800 222-1222) right away.

Directions

- adults and children 12 years and over: take 1 tablet every 4 hours. Do not take more than 6 tablets in 24 hours.
- children under 12 years: ask a doctor

Other Information

- each tablet contains: phosphorus 10 mg
- store at controlled room temperature between 20°-25°C (68°-77°F)
- protect from excessive moisture
- read all product information before using

Inactive Ingredients

Crosscarmellose Soidum, Colloidal Silicon Dioxide, Dicalcium Phosphate, FD&C Red 40, Magnesium Stearate, Microcrystalline Cellulose

Questions or comments?

Call + 1-848-235-5293

Monday through Friday 9AM – 4PM EST